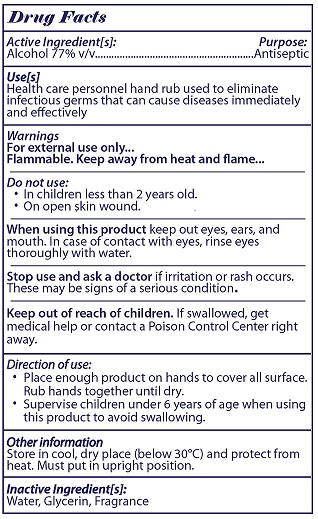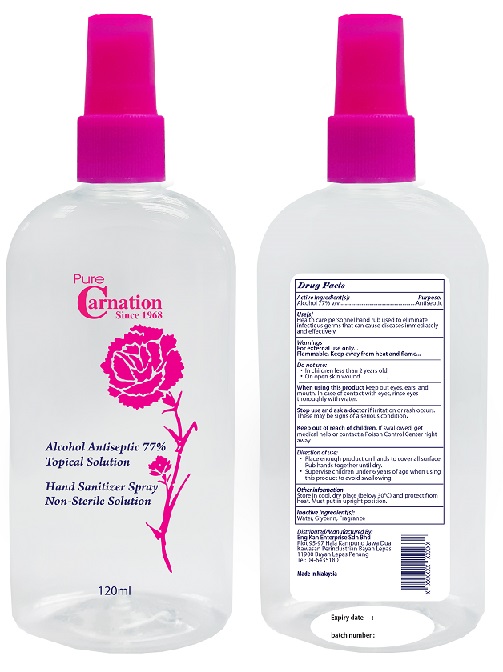 DRUG LABEL: Pure Carnation
NDC: 42498-002 | Form: LIQUID
Manufacturer: Eng Kah Enterprise Sdn.Bhd
Category: otc | Type: HUMAN OTC DRUG LABEL
Date: 20200610

ACTIVE INGREDIENTS: ALCOHOL 77 mL/100 mL
INACTIVE INGREDIENTS: WATER; GLYCERIN; FRAGRANCE LAVENDER & CHIA F-153480

Active Ingredient

Alcohol 77% v/v.

Purpose

Antiseptic

Use[s]

Health care personnel hand rub used to eliminate infectious germs that can cause diseases immediately and effectively.

Warnings

For external use only...

Flammable. Keep away from heat or flame...

Do not use:

- In children less than 2 years old.
- On open skin wound.

When using this product keep out eyes, ears, and mouth. In case of contact with eyes, rinse eyes thoroughly with water.

Stop use and ask a doctor if irritation or rash occurs. These may be signs of a serious condition.

Keep out of reach of children. If swallowed, get medical help or contact a Poison Control Center right away.

Directions

- Place enough product on hands to cover all surfaces. Rub hands together until dry.
- Supervise children under 6 years of age when using this product to avoid swallowing.

Other information

Store in cool, dry place (below 30^0C) and protect from heat. Must put in upright position.

Inactive ingredients

Water, Glycerin, Fragrance.